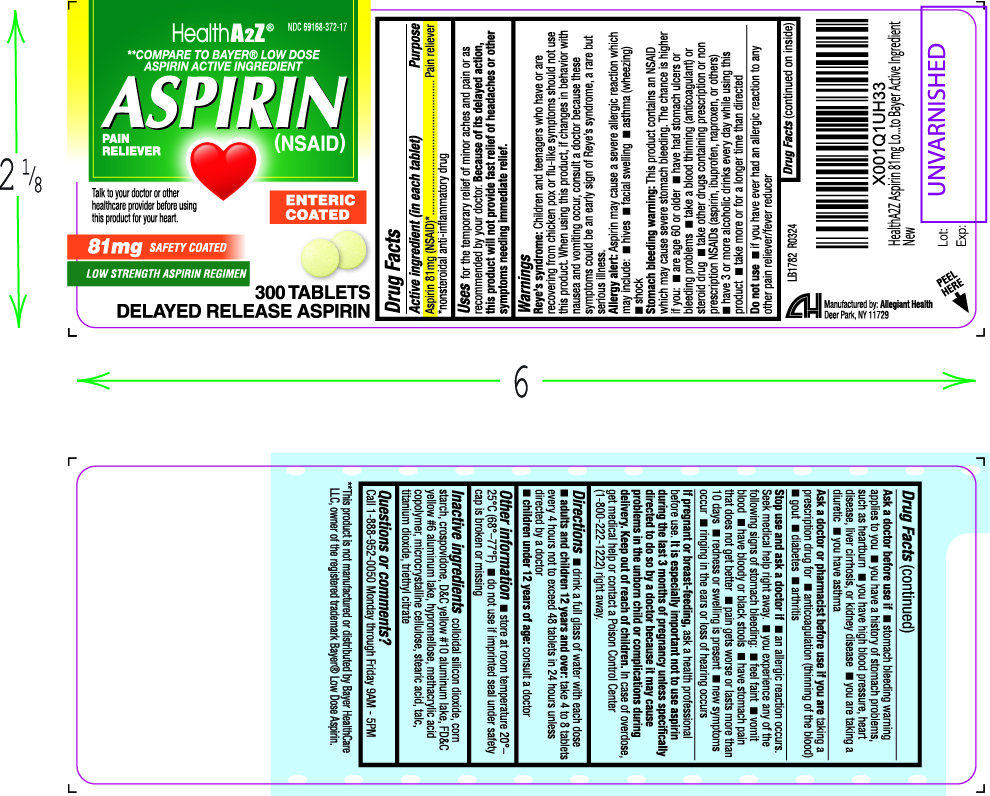 DRUG LABEL: Aspirin
NDC: 69168-372 | Form: TABLET
Manufacturer: Allegiant Health
Category: otc | Type: HUMAN OTC DRUG LABEL
Date: 20201111

ACTIVE INGREDIENTS: ASPIRIN 81 mg/1 1
INACTIVE INGREDIENTS: SILICON DIOXIDE; STARCH, CORN; CROSPOVIDONE; D&C YELLOW NO. 10 ALUMINUM LAKE; FD&C YELLOW NO. 6; HYPROMELLOSE, UNSPECIFIED; METHACRYLIC ACID - METHYL METHACRYLATE COPOLYMER (1:1); MICROCRYSTALLINE CELLULOSE; STEARIC ACID; TALC; TITANIUM DIOXIDE; TRIETHYL CITRATE

Drug Facts

Active ingredient

Aspirin 81 mg (NSAID*)
*nonsteroidal anti-inflammatory drug

Purpose

Pain reliever

Uses

for the temporary relief of minor aches and pains or as recommended by your doctor. Because of its delayed action, this product will not provide fast relief of headaches or other symptoms needing immediate relief.

Warnings

Reye’s syndrome:Children and teenagers who have or are recovering from chicken pox or flu-like symptoms should not use this product. When using this product, if changes in behavior with nausea and vomiting occur, consult a doctor because these symptoms could be an early sign of Reye’s syndrome, a rare but serious illness.

Allergy alert : Aspirin may cause a severe allergic reaction which may include hives, facial swelling, asthma (wheezing), shock.

Stomach bleeding warning: This product contains an NSAID, which may cause severe stomach bleeding. The chance is higher if you ■ are age 60 or older ■ have had stomach ulcers or bleeding problems ■ take a blood thinning (anticoagulant) or steroid drug ■ take other drugs containing prescription or nonprescription NSAIDs (aspirin, ibuprofen, naproxen, or others) ■ have 3 or more alcoholic drinks every day while using this product ■ take more or for a longer time than directed

Do not use

- if you have ever had an allergic reaction to any other pain reliever/fever reducer

Ask a doctor before use if

- stomach bleeding warning applies to you
- you have a history of stomach problems, such as heartburn
- you have high blood pressure, heart disease, liver cirrhosis, or kidney disease
- you are taking a diuretic
- you have asthma

Ask a doctor or pharmacist before use if you are

are taking a prescription drug for

- diabetes
- gout
- arthritis

Stop use and ask a doctor if

- an allergic reaction occurs. Seek medical help right away.
- you experience any of the following signs of stomach bleeding:
- feel faint
- vomit blood
- have bloody or black stools
- have stomach pain that does not get better
- pain gets worse or lasts more than10 days
- redness or swelling is present
- new symptoms occur
- ringing in the ears or loss of hearing occurs

If pregnant or breast-feeding

ask a health professional before use. It is especially important not to use aspirin during the last 3 months of pregnancy unless specifically directed to do so by a doctor because it may cause problems in the unborn child or complications during delivery.

Keep Out of Reach of Children

In case of accidental overdose, get medical help or contact a PoisonControl Center (1-800-222-1222) right away.

Directions

drink a full glass of water with each dose

adults and children 12 years and over: take 4 to 8 tablets every 4 hours not to exceed 48 tablets in 24 hours unless directed by a doctor

children under 12 years: consult a doctor

Other Information

- store at room temperature 20°– 25°C (68°–77°F)
- do not use if imprinted seal under safety cap is broken or missing

Inactive Ingredients

corn starch, crospovidone, D&C yellow #10 aluminum lake, FD&C yellow #6 aluminum
lake, hypromellose, methacrylic acid copolymer, microcrystalline cellulose, silicon
dioxide, stearic acid, talc, titanium dioxide, triethyl citrate

Questions and Comments

Call 1-888-952-0050 Monday through Friday 9AM - 5PM

Package/Label Principal Display Panel

Aspirin